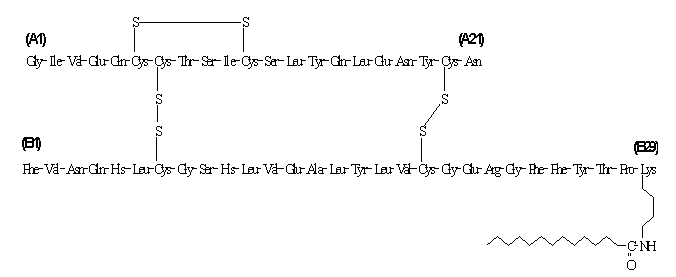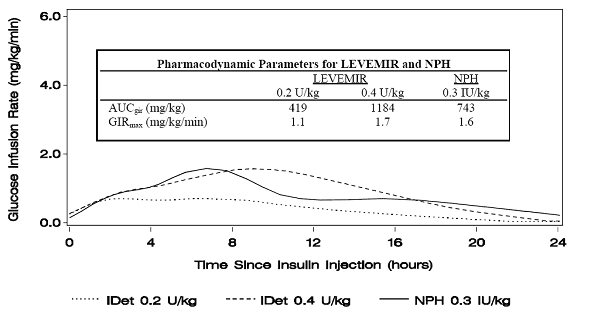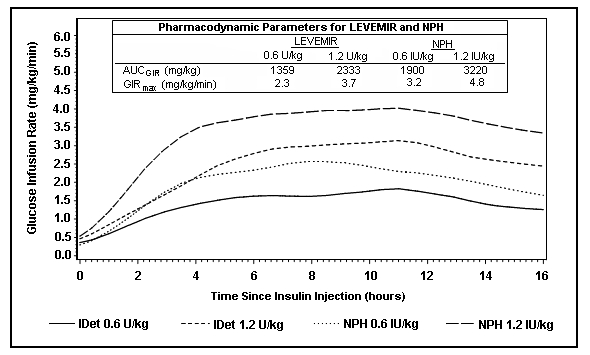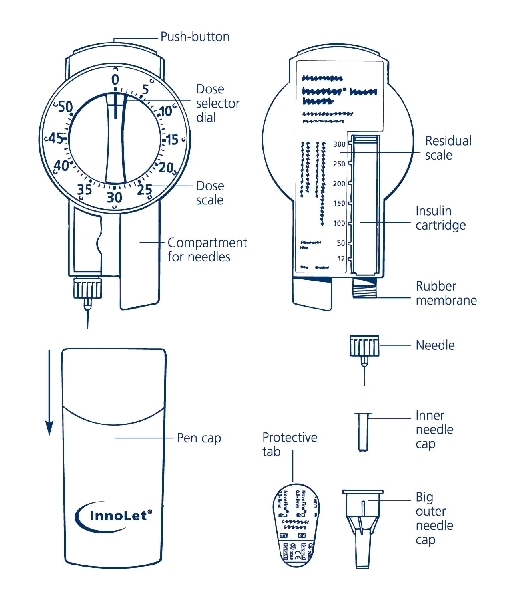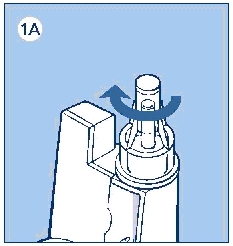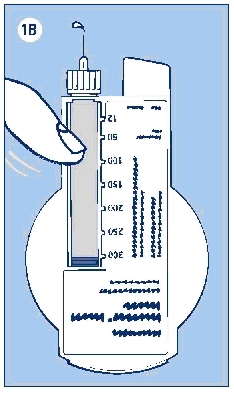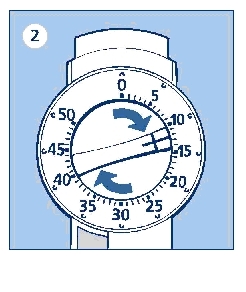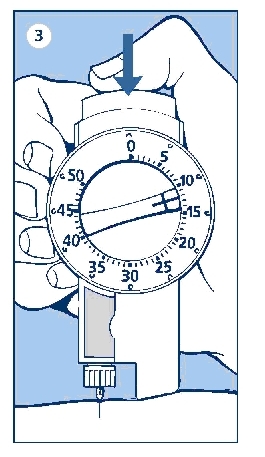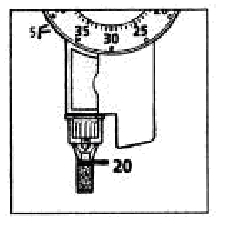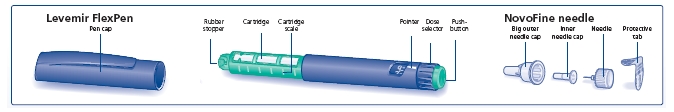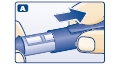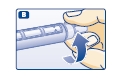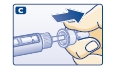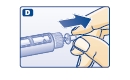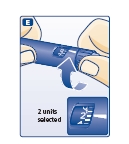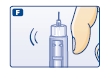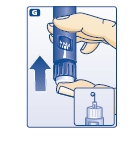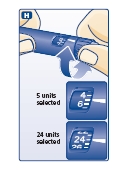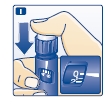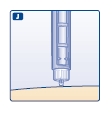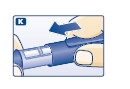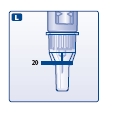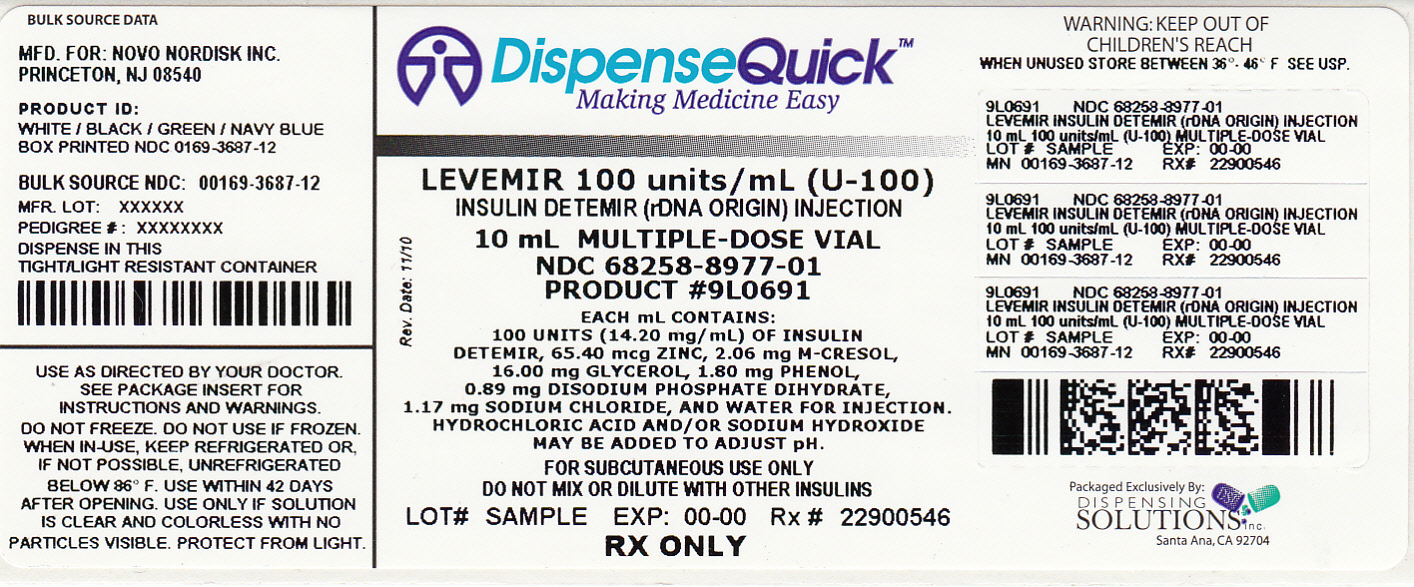 DRUG LABEL: Levemir
NDC: 68258-8977 | Form: IMPLANT
Manufacturer: Dispensing Solutions, Inc.
Category: prescription | Type: HUMAN PRESCRIPTION DRUG LABEL
Date: 20110914

ACTIVE INGREDIENTS: INSULIN DETEMIR 14.2 mg/1 mL
INACTIVE INGREDIENTS: HYDROCHLORIC ACID; GLYCERIN 16 mg/1 mL; METACRESOL 2.06 mg/1 mL; PHENOL 1.8 mg/1 mL; SODIUM CHLORIDE 1.17 mg/1 mL; SODIUM HYDROXIDE; SODIUM PHOSPHATE, DIBASIC, DIHYDRATE 0.89 mg/1 mL; ZINC 65.4 ug/1 mL

Levemir® (insulin detemir [rDNA origin] injection)

DESCRIPTION

LEVEMIR® (insulin detemir [rDNA origin] injection) is a sterile solution of insulin detemir for use as an injection. Insulin detemir is a long-acting basal insulin analog, with up to 24 hours duration of action, produced by a process that includes expression of recombinant DNA in Saccharomyces cerevisiae followed by chemical modification.

Insulin detemir differs from human insulin in that the amino acid threonine in position B30 has been omitted, and a C14 fatty acid chain has been attached to the amino acid B29. Insulin detemir has a molecular formula of C267H402O76N64S6 and a molecular weight of 5916.9. It has the following structure:

LEVEMIR is a clear, colorless, aqueous, neutral sterile solution. Each milliliter of LEVEMIR contains 100 U (14.2 mg/mL) insulin detemir, 65.4 mcg zinc, 2.06 mg m-cresol, 16.0 mg glycerol, 1.80 mg phenol, 0.89 mg disodium phosphate dihydrate, 1.17 mg sodium chloride, and water for injection. Hydrochloric acid and/or sodium hydroxide may be added to adjust pH. LEVEMIR has a pH of approximately 7.4.

CLINICAL PHARMACOLOGY

Mechanism of Action

The primary activity of insulin detemir is the regulation of glucose metabolism. Insulins, including insulin detemir, exert their specific action through binding to insulin receptors.

Receptor-bound insulin lowers blood glucose by facilitating cellular uptake of glucose into skeletal muscle and fat and by inhibiting the output of glucose from the liver. Insulin inhibits lipolysis in the adipocyte, inhibits proteolysis, and enhances protein synthesis.

Pharmacodynamics

Insulin detemir is a soluble, long-acting basal human insulin analog with a relatively flat action profile. The mean duration of action of insulin detemir ranged from 5.7 hours at the lowest dose to 23.2 hours at the highest dose (sampling period 24 hours).

The prolonged action of LEVEMIR is mediated by the slow systemic absorption of insulin detemir molecules from the injection site due to strong self-association of the drug molecules and albumin binding. Insulin detemir is distributed more slowly to peripheral target tissues since insulin detemir in the bloodstream is highly bound to albumin.

Figure 1 shows glucose infusion rate results from a glucose clamp study in patients with type 1 diabetes.

Figure 1: Activity Profiles in Patients with Type 1 Diabetes in a 24-hour Glucose Clamp Study

Figure 2 shows glucose infusion rate results from a 16-hour glucose clamp study in patients with type 2 diabetes. The clamp study was terminated at 16 hours according to protocol.

Figure 2: Activity Profiles in Patients with Type 2 Diabetes in a 16-hour Glucose Clamp Study

For doses in the interval of 0.2 to 0.4 U/kg, LEVEMIR exerts more than 50% of its maximum effect from 3 to 4 hours up to approximately 14 hours after dose administration.

In a glucose clamp study, the overall glucodynamic effect (AUCGIR 0-24h) [mean mg/kg ± SD (CV)] of four separate subcutaneous injections in the thigh was 1702.6 ± 489 mg/kg (29%) in the LEVEMIR group and 1922.8 ± 765 mg/kg (40%) for NPH. The clinical significance of this difference has not been established.

Pharmacokinetics

Absorption

After subcutaneous injection of insulin detemir in healthy subjects and in patients with diabetes, insulin detemir serum concentrations indicated a slower, more prolonged absorption over 24 hours in comparison to NPH human insulin.

Maximum serum concentration (Cmax) is reached between 6 and 8 hours after administration.

The absolute bioavailability of insulin detemir is approximately 60%.

Distribution and Elimination

More than 98% insulin detemir in the bloodstream is bound to albumin. LEVEMIR has a small apparent volume of distribution of approximately 0.1 L/kg. LEVEMIR, after subcutaneous administration, has a terminal half-life of 5 to7 hours depending on dose.

Special Populations

Children and Adolescents- The pharmacokinetic properties of LEVEMIR were investigated in children (6 to 12 years) and adolescents (13 to 17 years) and adults with type 1 diabetes. Similar to NPH human insulin, slightly higher plasma Area Under the Curve (AUC) and Cmax were observed in children by 10% and 24%, respectively, compared to adolescents and adults. There was no difference in pharmacokinetics between adolescents and adults.

Geriatrics- In a clinical trial investigating differences in pharmacokinetics of a single subcutaneous dose of LEVEMIR in young (25 to 35 years) versus elderly (≥68 years) healthy subjects, higher insulin AUC levels (up to 35%) were found in elderly subjects due to a reduced clearance. As with other insulin preparations, LEVEMIR should always be titrated according to individual requirements.

Gender- In controlled clinical trials, no clinically relevant difference between genders is seen in pharmacokinetic parameters based on subgroup analyses.

Race- In two trials in healthy Japanese and Caucasian subjects, there were no clinically relevant differences seen in pharmacokinetic parameters. Pharmacokinetics and pharmacodynamics of LEVEMIR were investigated in a clamp trial comparing patients with type 2 diabetes of Caucasian, African-American, and Latino origin. Dose-response relationships were comparable for LEVEMIR in these three populations.

Renal impairment- Individuals with renal impairment showed no difference in pharmacokinetic parameters as compared to healthy volunteers. However, literature reports have shown that clearance of human insulin is decreased in renally impaired patients. Careful glucose monitoring and dose adjustments of insulin, including LEVEMIR, may be necessary in patients with renal dysfunction (see PRECAUTIONS, Renal Impairment).

Hepatic impairment- Individuals with severe hepatic dysfunction, without diabetes, were observed to have lower AUCs as compared to healthy volunteers. Careful glucose monitoring and dose adjustments of insulin, including LEVEMIR, may be necessary in patients with hepatic dysfunction (see PRECAUTIONS, Hepatic Impairment).

Pregnancy- The effect of pregnancy on the pharmacokinetics and pharmacodynamics of LEVEMIR has not been studied (see PRECAUTIONS, Pregnancy).

Smoking- The effect of smoking on the pharmacokinetics and pharmacodynamics of LEVEMIR has not been studied.

CLINICAL STUDIES

The efficacy and safety of LEVEMIR given once-daily at bedtime or twice-daily (before breakfast and at bedtime, before breakfast and with the evening meal, or at 12-hour intervals) was compared to that of once-daily or twice-daily NPH human insulin or once-daily insulin glargine in non-blinded, randomized, parallel studies of 6004 patients with diabetes (3724 with type 1, and 2280 with type 2). In general, patients treated with LEVEMIR achieved levels of glycemic control similar to those treated with NPH human insulin or insulin glargine, as measured by glycosylated hemoglobin (HbA1c).

Type 1 Diabetes – Adult

In one non-blinded clinical study (Study A, n=409), adult patients with type 1 diabetes were randomized to treatment with either LEVEMIR at 12-hour intervals, LEVEMIR morning and bedtime or NPH human insulin morning and bedtime. Insulin aspart was also administered before each meal. At 16 weeks of treatment, the combined LEVEMIR-treated patients had similar HbA1c and fasting plasma glucose (FPG) reductions to NPH-treated patients (Table 1). Differences in timing of LEVEMIR administration (or flexible dosing) had no effect on HbA1c, FPG, body weight, or risk of having hypoglycemic episodes.

Overall glycemic control achieved with LEVEMIR was compared to that achieved with insulin glargine in a randomized, non-blinded, clinical study (Study B, n=320) in which patients with type 1 diabetes were treated for 26 weeks with either twice-daily (morning and bedtime) LEVEMIR or once-daily (bedtime) insulin glargine. Insulin aspart was administered before each meal. LEVEMIR-treated patients had a decrease in HbA1c similar to that of insulin glargine-treated patients.

In a randomized, controlled clinical study (Study C, n=749), patients with type 1 diabetes were treated with once-daily (bedtime) LEVEMIR or NPH human insulin, both in combination with human soluble insulin before each meal for 6 months. LEVEMIR and NPH human insulin had a similar effect on HbA1c.

Table 1: Efficacy and Insulin Dosage in Type 1 Diabetes Mellitus - Adult
 | Study A
Treatment duration | 16 weeks
Treatment in combination with | NovoLog® (insulin aspart)
 | LEVEMIR | NPH
Number of subjects treated | 276 | 133
HbA1c (%)
Baseline | 8.64 | 8.51
End of study adjusted mean | 7.76 | 7.94
Mean change from baseline | -0.82 | -0.60
Fasting Plasma Glucose (mg/dL)
End of study adjusted mean | 168 | 202
Mean change from baseline | -42.48 | -10.80
Daily Basal Insulin Dose (U/kg)
Prestudy mean | 0.36 | 0.39
End of study mean | 0.49 | 0.45
Daily Bolus Insulin Dose (U/kg)
Prestudy mean | 0.40 | 0.40
End of study mean | 0.38 | 0.38
Baseline values were included as covariates in an ANCOVA analysis.

Type 1 Diabetes - Pediatric

In a non-blinded, randomized, controlled clinical study (Study D, n=347), pediatric patients (age range 6 to 17) with type 1 diabetes were treated for 26 weeks with a basal-bolus insulin regimen. LEVEMIR and NPH human insulin were administered once- or twice-daily (bedtime or morning and bedtime) according to pretrial dose regimen. Bolus insulin aspart was administered before each meal. LEVEMIR-treated patients had a decrease in HbA1c similar to that of NPH human insulin.

Table 2: Efficacy and Insulin Dosage in Type 1 Diabetes Mellitus - Pediatric
 | Study D
Treatment duration | 26 weeks
Treatment in combination with | NovoLog® (insulin aspart)
 | LEVEMIR | NPH
Number of subjects treated | 232 | 115
HbA1c (%)
Baseline | 8.75 | 8.77
End of study adjusted mean | 8.02 | 7.93
Mean change from baseline | -0.72 | -0.80
Fasting Plasma Glucose (mg/dL)
End of study adjusted mean | 151.92 | 172.44
Mean change from baseline | -45.00 | -19.98
Daily Basal Insulin Dose (U/kg)
Prestudy mean | 0.48 | 0.49
End of study mean | 0.67 | 0.64
Daily Bolus Insulin Dose (U/kg)
Prestudy mean | 0.52 | 0.47
End of study mean | 0.52 | 0.51

Type 2 Diabetes – Adult

In a 24-week, non-blinded, randomized, clinical study (Study E, n=476), LEVEMIR administered twice-daily (before breakfast and evening) was compared to a similar regimen of NPH human insulin as part of a regimen of combination therapy with one or two of the following oral antidiabetes agents (metformin, insulin secretagogue, or α–glucosidase inhibitor). LEVEMIR and NPH similarly lowered HbA1c from baseline (Table 3).

Table 3: Efficacy and Insulin Dosage in Type 2 Diabetes Mellitus
 | Study E
Treatment duration | 24 weeks
Treatment in combination with | OAD
 | LEVEMIR | NPH
Number of subjects treated | 237 | 239
HbA1c (%)
Baseline | 8.61 | 8.51
End of study adjusted mean | 6.58 | 6.46
Mean change from baseline | -1.84 | -1.90
Proportion achieving HbA1c ≤ 7% | 70% | 74%
Fasting Plasma Glucose (mg/dL)
End of study adjusted mean | 119.16 | 113.40
Mean change from baseline | -75.96 | -74.34
Daily Insulin Dose (U/kg)
End of study mean | 0.77 | 0.52

In a 22-week, non-blinded, randomized, clinical study (Study F, n=395) in adults with Type 2 diabetes, LEVEMIR and NPH human insulin were given once- or twice-daily as part of a basal-bolus regimen. As measured by HbA1c or FPG, LEVEMIR had efficacy similar to NPH human insulin.

INDICATIONS AND USAGE

LEVEMIR is indicated for once- or twice-daily subcutaneous administration for the treatment of adult and pediatric patients with type 1 diabetes mellitus or adult patients with type 2 diabetes mellitus who require basal (long acting) insulin for the control of hyperglycemia.

CONTRAINDICATIONS

LEVEMIR is contraindicated in patients hypersensitive to insulin detemir or one of its excipients.

WARNINGS

Hypoglycemia is the most common adverse effect of insulin therapy, including LEVEMIR. As with all insulins, the timing of hypoglycemia may differ among various insulin formulations.

Glucose monitoring is recommended for all patients with diabetes.

LEVEMIR is not to be used in insulin infusion pumps.

Any change of insulin dose should be made cautiously and only under medical supervision. Changes in insulin strength, timing of dosing, manufacturer, type (e.g., regular, NPH, or insulin analogs), species (animal, human), or method of manufacture (rDNA versus animal-source insulin) may result in the need for a change in dosage.

Concomitant oral antidiabetic treatment may need to be adjusted.

Needles and Levemir FlexPen must not be shared.

PRECAUTIONS

General

Inadequate dosing or discontinuation of treatment may lead to hyperglycemia and, in patients with type 1 diabetes, diabetic ketoacidosis. The first symptoms of hyperglycemia usually occur gradually over a period of hours or days. They include nausea, vomiting, drowsiness, flushed dry skin, dry mouth, increased urination, thirst and loss of appetite as well as acetone breath. Untreated hyperglycemic events are potentially fatal.

LEVEMIR is not intended for intravenous or intramuscular administration. The prolonged duration of activity of insulin detemir is dependent on injection into subcutaneous tissue. Intravenous administration of the usual subcutaneous dose could result in severe hypoglycemia. Absorption after intramuscular administration is both faster and more extensive than absorption after subcutaneous administration.

LEVEMIR should not be diluted or mixed with any other insulin preparations (see PRECAUTIONS, Mixing of Insulins).

Insulin may cause sodium retention and edema, particularly if previously poor metabolic control is improved by intensified insulin therapy.

Lipodystrophy and hypersensitivity are among potential clinical adverse effects associated with the use of all insulins.

As with all insulin preparations, the time course of LEVEMIR action may vary in different individuals or at different times in the same individual and is dependent on site of injection, blood supply, temperature, and physical activity.

Adjustment of dosage of any insulin may be necessary if patients change their physical activity or their usual meal plan.

Hypoglycemia

As with all insulin preparations, hypoglycemic reactions may be associated with the administration of LEVEMIR. Hypoglycemia is the most common adverse effect of insulins. Early warning symptoms of hypoglycemia may be different or less pronounced under certain conditions, such as long duration of diabetes, diabetic nerve disease, use of medications such as beta-blockers, or intensified diabetes control (see PRECAUTIONS, Drug Interactions). Such situations may result in severe hypoglycemia (and, possibly, loss of consciousness) prior to patients’ awareness of hypoglycemia.

The time of occurrence of hypoglycemia depends on the action profile of the insulins used and may, therefore, change when the treatment regimen or timing of dosing is changed. In patients being switched from other intermediate or long-acting insulin preparations to once- or twice-daily LEVEMIR, dosages can be prescribed on a unit-to-unit basis; however, as with all insulin preparations, dose and timing of administration may need to be adjusted to reduce the risk of hypoglycemia (see DOSAGE AND ADMINISTRATION, Changeover to LEVEMIR).

Renal Impairment

As with other insulins, the requirements for LEVEMIR may need to be adjusted in patients with renal impairment (see CLINICAL PHARMACOLOGY, Pharmacokinetics).

Hepatic Impairment

As with other insulins, the requirements for LEVEMIR may need to be adjusted in patients with hepatic impairment (see CLINICAL PHARMACOLOGY, Pharmacokinetics).

Injection Site and Allergic Reactions

As with any insulin therapy, lipodystrophy may occur at the injection site and delay insulin absorption. Other injection site reactions with insulin therapy may include redness, pain, itching, hives, swelling, and inflammation. Continuous rotation of the injection site within a given area may help to reduce or prevent these reactions. Reactions usually resolve in a few days to a few weeks. On rare occasions, injection site reactions may require discontinuation of LEVEMIR.

In some instances, these reactions may be related to factors other than insulin, such as irritants in a skin cleansing agent or poor injection technique.

Systemic allergy: Generalized allergy to insulin, which is less common but potentially more serious, may cause rash (including pruritus) over the whole body, shortness of breath, wheezing, reduction in blood pressure, rapid pulse, or sweating. Severe cases of generalized allergy, including anaphylactic reaction, may be life-threatening.

Intercurrent Conditions

Insulin requirements may be altered during intercurrent conditions such as illness, emotional disturbances, or other stresses.

Information for Patients

LEVEMIR must only be used if the solution appears clear and colorless with no visible particles (see DOSAGE AND ADMINISTRATION, Preparation and Handling). Patients should be informed about potential risks and advantages of LEVEMIR therapy, including the possible side effects. Patients should be offered continued education and advice on insulin therapies, injection technique, life-style management, regular glucose monitoring, periodic glycosylated hemoglobin testing, recognition and management of hypo- and hyperglycemia, adherence to meal planning, complications of insulin therapy, timing of dosage, instruction for use of injection devices and proper storage of insulin. Patients should be informed that frequent, patient-performed blood glucose measurements are needed to achieve effective glycemic control to avoid both hyperglycemia and hypoglycemia. Patients must be instructed on handling of special situations such as intercurrent conditions (illness, stress, or emotional disturbances), an inadequate or skipped insulin dose, inadvertent administration of an increased insulin dose, inadequate food intake, or skipped meals. Refer patients to the LEVEMIR "Patient Information" circular for additional information.

As with all patients who have diabetes, the ability to concentrate and/or react may be impaired as a result of hypoglycemia or hyperglycemia.

Patients with diabetes should be advised to inform their health care professional if they are pregnant or are contemplating pregnancy (see PRECAUTIONS, Pregnancy).

Laboratory Tests

As with all insulin therapy, the therapeutic response to LEVEMIR should be monitored by periodic blood glucose tests. Periodic measurement of HbA1c is recommended for the monitoring of long-term glycemic control.

Drug Interactions

A number of substances affect glucose metabolism and may require insulin dose adjustment and particularly close monitoring.

The following are examples of substances that may reduce the blood-glucose-lowering effect of insulin: corticosteroids, danazol, diuretics, sympathomimetic agents (e.g., epinephrine, albuterol, terbutaline), isoniazid, phenothiazine derivatives, somatropin, thyroid hormones, estrogens, progestogens (e.g., in oral contraceptives).

The following are examples of substances that may increase the blood-glucose-lowering effect of insulin and susceptibility to hypoglycemia: oral antidiabetic drugs, ACE inhibitors, disopyramide, fibrates, fluoxetine, MAO inhibitors, propoxyphene, salicylates, somatostatin analog (e.g., octreotide), and sulfonamide antibiotics.

Beta-blockers, clonidine, lithium salts, and alcohol may either potentiate or weaken the blood-glucose-lowering effect of insulin. Pentamidine may cause hypoglycemia, which may sometimes be followed by hyperglycemia. In addition, under the influence of sympatholytic medicinal products such as beta-blockers, clonidine, guanethidine, and reserpine, the signs of hypoglycemia may be reduced or absent.

The results of in-vitro and in-vivo protein binding studies demonstrate that there is no clinically relevant interaction between insulin detemir and fatty acids or other protein bound drugs.

Mixing of Insulins

If LEVEMIR is mixed with other insulin preparations, the profile of action of one or both individual components may change. Mixing LEVEMIR with insulin aspart, a rapid acting insulin analog, resulted in about 40% reduction in AUC(0-2h) and Cmax for insulin aspart compared to separate injections when the ratio of insulin aspart to LEVEMIR was less than 50%.

LEVEMIR should NOT be mixed or diluted with any other insulin preparations.

Carcinogenesis, Mutagenesis, Impairment of Fertility

Standard 2-year carcinogenicity studies in animals have not been performed. Insulin detemir tested negative for genotoxic potential in the in-vitro reverse mutation study in bacteria, human peripheral blood lymphocyte chromosome aberration test, and the in-vivo mouse micronucleus test.

Preganancy Category C

Teratogenic effects

In a fertility and embryonic development study, insulin detemir was administered to female rats before mating, during mating, and throughout pregnancy at doses up to 300 nmol/kg/day (3 times the recommended human dose, based on plasma Area Under the Curve (AUC) ratio). Doses of 150 and 300 nmol/kg/day produced numbers of litters with visceral anomalies. Doses up to 900 nmol/kg/day (approximately 135 times the recommended human dose based on AUC ratio) were given to rabbits during organogenesis. Drug-dose related increases in the incidence of fetuses with gall bladder abnormalities such as small, bilobed, bifurcated and missing gall bladders were observed at a dose of 900 nmol/kg/day. The rat and rabbit embryofetal development studies that included concurrent human insulin control groups indicated that insulin detemir and human insulin had similar effects regarding embryotoxicity and teratogenicity.

Nursing mothers

It is unknown whether LEVEMIR is excreted in significant amounts in human milk. For this reason, caution should be exercised when LEVEMIR is administered to a nursing mother. Patients with diabetes who are lactating may require adjustments in insulin dose, meal plan, or both.

Pediatric use

In a controlled clinical study, HbA1c concentrations and rates of hypoglycemia were similar among patients treated with LEVEMIR and patients treated with NPH human insulin.

Geriatric use

Of the total number of subjects in intermediate and long-term clinical studies of LEVEMIR, 85 (type 1 studies) and 363 (type 2 studies) were 65 years and older. No overall differences in safety or effectiveness were observed between these subjects and younger subjects, and other reported clinical experience has not identified differences in responses between the elderly and younger patients, but greater sensitivity of some older individuals cannot be ruled out. In elderly patients with diabetes, the initial dosing, dose increments, and maintenance dosage should be conservative to avoid hypoglycemic reactions. Hypoglycemia may be difficult to recognize in the elderly.

ADVERSE REACTIONS

Adverse events commonly associated with human insulin therapy include the following:

Body as Whole: allergic reactions (see PRECAUTIONS, Allergy).

Skin and Appendages: lipodystrophy, pruritus, rash. Mild injection site reactions occurred more frequently with LEVEMIR than with NPH human insulin and usually resolved in a few days to a few weeks (see PRECAUTIONS, Allergy).

Other:

Hypoglycemia: (see WARNINGS and PRECAUTIONS).

In trials of up to 6 months duration in patients with type 1 and type 2 diabetes, the incidence of severe hypoglycemia with LEVEMIR was comparable to the incidence with NPH, and, as expected, greater overall in patients with type 1 diabetes (Table 4).

Weight gain:

In trials of up to 6 months duration in patients with type 1 and type 2 diabetes, LEVEMIR was associated with somewhat less weight gain than NPH (Table 4). Whether these observed differences represent true differences in the effects of LEVEMIR and NPH insulin is not known, since these trials were not blinded and the protocols (e.g., diet and exercise instructions and monitoring) were not specifically directed at exploring hypotheses related to weight effects of the treatments compared. The clinical significance of the observed differences has not been established.

Table 4: Safety Information on Clinical Studies
 |  |  | Weight (kg) |  | Hypoglycemia (events/subject/month)
 | Treatment | # of subjects | Baseline | End of treatment | Major | Minor
Type 1
Study A | LEVEMIR | N=276 | 75.0 | 75.1 | 0.045 | 2.184
Study A | NPH | N=133 | 75.7 | 76.4 | 0.035 | 3.063
Study C | LEVEMIR | N=492 | 76.5 | 76.3 | 0.029 | 2.397
Study C | NPH | N=257 | 76.1 | 76.5 | 0.027 | 2.564
Study D Pediatric | LEVEMIR | N=232 | N/A | N/A | 0.076 | 2.677
Study D Pediatric | NPH | N=115 | N/A | N/A | 0.083 | 3.203
Type 2
Study E | LEVEMIR | N=237 | 82.7 | 83.7 | 0.001 | 0.306
Study E | NPH | N=239 | 82.4 | 85.2 | 0.006 | 0.595
Study F | LEVEMIR | N=195 | 81.8 | 82.3 | 0.003 | 0.193
Study F | NPH | N=200 | 79.6 | 80.9 | 0.006 | 0.235

OVERDOSAGE

Hypoglycemia may occur as a result of an excess of insulin relative to food intake, energy expenditure, or both. Mild episodes of hypoglycemia usually can be treated with oral glucose. Adjustments in drug dosage, meal patterns, or exercise may be needed. More severe episodes with coma, seizure, or neurologic impairment may be treated with intramuscular/subcutaneous glucagon or concentrated intravenous glucose. After apparent clinical recovery from hypoglycemia, continued observation and additional carbohydrate intake may be necessary to avoid reoccurrence of hypoglycemia.

DOSAGE AND ADMINISTRATION

LEVEMIR can be administered once- or twice-daily. The dose of LEVEMIR should be adjusted according to blood glucose measurements. The dosage of LEVEMIR should be individualized based on the physician’s advice, in accordance with the needs of the patient.

- For patients treated with Levemir once-daily, the dose should be administered with the evening meal or at bedtime.
- For patients who require twice-daily dosing for effective blood glucose control, the evening dose can be administered either with the evening meal, at bedtime, or 12 hours after the morning dose.

LEVEMIR should be administered by subcutaneous injection in the thigh, abdominal wall, or upper arm. Injection sites should be rotated within the same region. As with all insulins, the duration of action will vary according to the dose, injection site, blood flow, temperature, and level of physical activity.

Dose Determination for LEVEMIR

- For patients with type 1 or type 2 diabetes on basal-bolus treatment, changing the basal insulin to LEVEMIR can be done on a unit-to-unit basis. The dose of LEVEMIR should then be adjusted to achieve glycemic targets. In some patients with type 2 diabetes, more LEVEMIR may be required than NPH insulin. In a clinical study, the mean dose at end of treatment was 0.77 U/kg for LEVEMIR and 0.52 IU/kg for NPH human insulin (see Table 3).
- For patients currently receiving only basal insulin, changing the basal insulin to LEVEMIR can be done on a unit-to-unit basis.
- For insulin-naïve patients with type 2 diabetes who are inadequately controlled on oral antidiabetic drugs, LEVEMIR should be started at a dose of 0.1 to 0.2 U/kg once-daily in the evening or 10 units once- or twice-daily, and the dose adjusted to achieve glycemic targets.
- As with all insulins, close glucose monitoring is recommended during the transition and in the initial weeks thereafter. Dose and timing of concurrent short-acting insulins or other concomitant antidiabetic treatment may need to be adjusted.

Preparation and Handling

LEVEMIR should be inspected visually prior to administration and should only be used if the solution appears clear and colorless.

LEVEMIR should not be mixed or diluted with any other insulin preparations.

After each injection, patients must remove the needle without recapping and dispose of it in a puncture-resistant container. Used syringes, needles, or lancets should be placed in “sharps” containers (such as red biohazard containers), hard plastic containers (such as detergent bottles), or metal containers (such as an empty coffee can). Such containers should be sealed and disposed of properly.

HOW SUPPLIED

LEVEMIR is available in the following package sizes: each presentation containing 100 Units of insulin detemir per mL (U-100).

10 mL vial | NDC 0169-3687-12
3 mL PenFill® cartridges* | NDC 0169-3305-11
3 mL InnoLet® | NDC 0169-2312-11
3 mL FlexPen® | NDC 0169-6439-10

*LEVEMIR PenFill® cartridges are for use with Novo Nordisk 3 mL PenFill® cartridge compatible insulin delivery devices and NovoFine® disposable needles.

RECOMMENDED STORAGE

Unused LEVEMIR should be stored between 2° and 8°C (36° to 46° F). Do not freeze. Do not use LEVEMIR if it has been frozen.

Vials:

After initial use, vials should be stored in a refrigerator, never in a freezer. If refrigeration is not possible, the in-use vial can be kept unrefrigerated at room temperature, below 30°C (86°F), for up to 42 days, as long as it is kept as cool as possible and away from direct heat and light.

Unpunctured vials can be used until the expiration date printed on the label if they are stored in a refrigerator. Keep unused vials in the carton so they will stay clean and protected from light.

PenFill® cartridges, FlexPen® or InnoLet®:

After initial use, a cartridge (PenFill®) or a prefilled syringe (including FlexPen® or InnoLet®) may be used for up to 42 days if it is kept at room temperature, below 30°C (86°F). In-use cartridges and prefilled syringes in-use must NOT be stored in a refrigerator and must NOT be stored with the needle in place. Keep all cartridges and prefilled syringes away from direct heat and sunlight.

Not in-use (unopened) LEVEMIR PenFill®, FlexPen® or InnoLet® can be used until the expiration date printed on the label if they are stored in a refrigerator. Keep unused cartridges and prefilled syringes in the carton so they will stay clean and protected from light.

The storage conditions are summarized in the following table:

 | Not in-use (unopened); Room Temperature; (below 30°C) | Not in-use; (unopened); Refrigerated | In-use (opened); Room Temperature; (below 30°C)
10 mL vial | 42 days | Until expiration date | 42 days; refrigerated/room temperature
3 mL PenFill® cartridges | 42 days | Until expiration date | 42 days (Do not refrigerate)
3 mL InnoLet® | 42 days | Until expiration date | 42 days (Do not refrigerate)
3 mL FlexPen® | 42 days | Until expiration date | 42 days (Do not refrigerate)

Date of issue: July 15, 2009

Version: 5

Novo Nordisk®, Levemir®, NovoLog®, FlexPen®, InnoLet®, PenFill®, and NovoFine® are registered trademarks owned by Novo Nordisk A/S.

© 2005/2009 Novo Nordisk Inc.

Levemir® is covered by US Patent Nos. 5,750,497; 5,866,538; 6,011,007; 6,869,930 and other patents pending.

FlexPen® is covered by US Patent Nos. 6,004,297; 6,235,004; 6,582,404 and other patents pending.

Manufactured for:

Novo Nordisk Inc.

Princeton, NJ 08540

www.novonordisk-us.com

Manufactured by:

Novo Nordisk A/S

DK-2880 Bagsvaerd, Denmark

PATIENT INFORMATION

Levemir® (LEV–uh-mere)

(insulin detemir [rDNA origin] injection)

Important:

Know your insulin. Do not change the type of insulin you use unless told to do so by your healthcare provider. The amount of insulin you take as well as the best time for you to take your insulin may need to change if you take a different type of insulin.
Make sure you know the type and strength of insulin prescribed for you.
Read the Patient Information that comes with Levemir before you start taking it and each time you get a refill. There may be new information. This leaflet does not take the place of talking with your healthcare provider about your diabetes or your treatment. Make sure that you know how to manage your diabetes. Ask your healthcare provider if you have any questions about managing your diabetes.

What is Levemir?

Levemir is a man-made long-acting insulin that is used to control high blood sugar in adults and children with diabetes mellitus.

Who should not use Levemir?

Do not take Levemir if:

- Your blood sugar is too low (hypoglycemia).
- You are allergic to anything in Levemir. See the end of this leaflet for a complete list of ingredients in Levemir. Check with your healthcare provider if you are not sure.

Tell your healthcare provider:

- about all of your medical conditions. Medical conditions can affect your insulin needs and your dose of Levemir.
- if you are pregnant or breast-feeding. You and your healthcare provider should talk about the best way to manage your diabetes while you are pregnant or breastfeeding. Levemir has not been studied in pregnant or nursing women.
- about all medicines you take, including prescriptions and non-prescription medicines, vitamins and herbal supplements. Your Levemir dose may change if you take other medicines.

Know the medicines you take. Keep a list of your medicines with you to show your healthcare provider when you get a new medicine.
How should I take Levemir?
Only use Levemir if it appears clear and colorless. There may be air bubbles. This is normal. If it looks cloudy, thickened, or colored, or if it contains solid particles do not use it and call Novo Nordisk at 1-800-727-6500.
Levemir comes in:

- 10 mL vials (small bottles) for use with a syringe
- 3 mL PenFill® cartridges for use with the Novo Nordisk 3 mL PenFill cartridge compatible insulin delivery devices and NovoFine® disposable needles. The cartridge delivery device can be used with a NovoPen® 3 PenMate®
- 3 mL Levemir FlexPen®
- 3 mL Levemir InnoLet

Read the instructions for use that come with your Levemir product. Talk to your healthcare provider if you have any questions. Your healthcare provider should show you how to inject Levemir before you start taking it.

- Take Levemir exactly as prescribed.
- Levemir is a long-acting insulin. The effect of Levemir may last up to 24 hours after injection.
- Inject Levemir into the skin of your stomach area, upper arms, or thighs. Levemir may affect your blood sugar levels sooner if you inject it into the skin of your stomach area or upper arm. Never inject Levemir into a vein or into a muscle.
- Change (rotate) your injection site within the chosen area (for example, stomach or upper arm) with each dose. Do not inject into the exact same spot for each injection.
- If you take too much Levemir, your blood sugar may fall low (hypoglycemia). You can treat mild low blood sugar (hypoglycemia) by drinking or eating something sugary right away (fruit juice, sugar candies, or glucose tablets). It is important to treat low blood sugar (hypoglycemia) right away because it could get worse and you could pass out (become unconscious). If you pass out you will need help from another person or emergency medical services right away, and will need treatment with a glucagon injection or treatment at a hospital. See “What are the possible side effects of Levemir?” for more information on low blood sugar (hypoglycemia).
- If you forget to take your dose of Levemir, your blood sugar may go too high (hyperglycemia). If high blood sugar (hyperglycemia) is not treated it can lead to serious problems, like loss of consciousness (passing out), coma or even death. Follow your healthcare provider’s instructions for treating high blood sugar. Know your symptoms of high blood sugar which may include:

- increased thirst

- a hard time breathing

- frequent urination

- fruity smell on the breath

- drowsiness

- high amounts of sugar and ketones in your urine

- loss of appetite

- nausea, vomiting (throwing up) or stomach pain

- Check your blood sugar levels. Ask your healthcare provider what your blood sugars should be and when you should check your blood sugar levels.
- Never mix Levemir with other insulin products.
- Never use Levemir in an insulin pump.

Your insulin dosage may need to change because of:

- illness

- change in diet

- stress

- change in physical activity or exercise

- other medicines you take

What should I avoid while using Levemir?

- Alcohol. Alcohol, including beer and wine, may affect your blood sugar when you take Levemir.
- Driving and operating machinery. You may have difficulty concentrating or reacting if you have low blood sugar (hypoglycemia). Be careful when you drive a car or operate machinery. Ask your healthcare provider if it is alright to drive if you often have:
-
  - low blood sugar
  - decreased or no warning signs of low blood sugar

What are the possible side effects of Levemir?

- low blood sugar (hypoglycemia). Symptoms of low blood sugar may include:

- sweating

- trouble concentrating or confusion

- dizziness or lightheadedness

- blurred vision

- shakiness

- slurred speech

- hunger

- anxiety, irritability or mood changes

- fast heart beat

- headache

- tingling of lips and tongue

Severe low blood sugar can cause unconsciousness (passing out), seizures, and death. Know your symptoms of low blood sugar. Follow your healthcare provider’s instructions for treating low blood sugar. Talk to your healthcare provider if low blood sugar is a problem for you.

- Serious allergic reaction (whole body reaction). Get medical help right away, if you develop a rash over your whole body, have trouble breathing, a fast heartbeat, or sweating.
- Reactions at the injection site (local allergic reaction). You may get redness, swelling, and itching at the injection site. If you keep having skin reactions or they are serious, talk to your healthcare provider. You may need to stop using Levemir and use a different insulin. Do not inject insulin into skin that is red, swollen, or itchy.
- Skin thickens or pits at the injection site (lipodystrophy). Change (rotate) where you inject your insulin to help to prevent these skin changes from happening. Do not inject insulin into this type of skin.
- Swelling of your hands and feet.
- Vision changes
- Low potassium in your blood (hypokalemia)

These are not all of the possible side effects from Levemir. Ask your healthcare provider or pharmacist for more information.
Call your healthcare provider for medical advice about side effects. You may report side effects to FDA at 1-800-FDA-1088.
How should I store Levemir?
All Unopened Levemir:

- Keep all unopened Levemir in the refrigerator between 36° to 46°F (2° to 8°C).
- Do not freeze. Do not use Levemir if it has been frozen.
- Keep unopened Levemir in the carton to protect from light.

Levemir in use:

- Vials
-
  - Keep in the refrigerator or at room temperature below 86°F (30°C) for up to 42 days.
  - Keep vials away from direct heat or light.
  - Throw away an opened vial after 42 days of use, even if there is insulin left in the vial.
  - Unopened vials can be used until the expiration date on the Levemir label, if the medicine has been stored in a refrigerator.
- Levemir FlexPen
-
  - Keep at room temperature below 86°F (30°C) for up to 42 days.
  - Do not store a Levemir FlexPen that you are using in the refrigerator.
  - Keep Levemir FlexPen away from direct heat or light.
  - Throw away a used Levemir FlexPen after 42 days, even if there is insulin left in the syringe.

General advice about Levemir
Medicines are sometimes prescribed for conditions that are not mentioned in the patient leaflet. Do not use Levemir for a condition for which it was not prescribed. Do not give Levemir to other people, even if they have the same symptoms you have. It may harm them.
This leaflet summarizes the most important information about Levemir. If you would like more information about Levemir or diabetes, talk with your healthcare provider. You can ask your healthcare provider or pharmacist for information about Levemir that is written for healthcare professionals. Call 1-800-727-6500 or visit www.novonordisk-us.com for more information.
Helpful information for people with diabetes is published by the American Diabetes Association, 1701 N Beauregard Street, Alexandria, VA 22311 and on www.diabetes.org.
Levemir ingredients include:

- Insulin detemir

- Zinc

- Glycerol

- Disodium hydrogen phosphate dihydrate

- Phenol

- Sodium chloride

- Water for injection

- Metacresol

- Hydrochloric acid or sodium hydroxide

All Levemir vials and Levemir FlexPen are latex free.
Date of Issue: May 22, 2009
Version: 4
Levemir® , PenFill® , FlexPen® , NovoPen® , NovoFine® , PenMate® , are trademarks of Novo Nordisk A/S.
Levemir® is covered by US Patent Nos. 5,750,497, 5,866,538, 6,011,007, 6,869,930, and other patents pending.
FlexPen® is covered by US Patent Nos. 6,582,404, 6,004,297, 6,235,004, and other patents pending.
PenFill® is covered by US Patent Nos. 6,126,646, 5,693,027, DES 347894, and other patents pending.
© 2005-2009 Novo Nordisk Inc.
Manufactured by:
Novo Nordisk A/S
DK-2880 Bagsvaerd, Denmark
For information about Levemir® contact:
Novo Nordisk Inc.
100 College Road West,
Princeton, New Jersey 08540
INSTRUCTIONS FOR USE
Levemir® 10 mL vial (100 units/mL, U-100)
Levemir® 3 mL PenFill® cartridge (100 units/mL, U-100)
How should I prepare and deliver the injection using different delivery devices?
Using the 10 mL vial:

1. At your first use, remove the tamper-resistant cap from the vial. If the cap has already been removed, do not use this vial and return it to your pharmacy.
2. Wipe the rubber membrane with an alcohol swab.
3. Do not roll or shake the vial. Vigorous shaking right before the dose is drawn into the syringe may cause bubbles or froth, which could cause dosage errors. The insulin should be used only if it is clear and colorless.
4. Pull back the plunger on your syringe until the black tip reaches the marking for the number of units you will inject.
5. Push the needle through the rubber membrane into the vial.
6. Push the plunger all the way in. This inserts air into the vial.
7. Turn the vial and syringe upside down together and slowly pull the plunger back to a few units beyond the correct dose.
8. If there are air bubbles, tap the syringe gently with your finger to raise the air bubbles to the needle. Then slowly push the plunger to the correct unit marking.
9. Lift the vial off the syringe.
10. Inject right away.
11. The syringe and vial should be disposed of properly without recapping the needle. After each injection, patients must remove the needle without recapping and dispose of it in a puncture-resistant container. Used syringes, needles, or lancets should be placed in sharps containers (such as red biohazard containers), hard plastic containers (such as detergent bottles), or metal containers (such as an empty coffee can). Such containers should be sealed and disposed of properly.

Using the LEVEMIR 3 mL PenFill® cartridge in 3 mL PenFill® cartridge delivery devices* (*see 3 mL PenFill® cartridge compatible delivery devices section):

1. Read the instruction manuals for the 3 mL PenFill® cartridge compatible delivery device* before the device is used.
2. The insulin should be used only if it is clear and colorless. Insert the PenFill® cartridge into the 3 mL PenFill® cartridge compatible delivery device*.
3. Place the needle onto the 3 mL PenFill® cartridge compatible delivery device* immediately before use
4. Airshots should be done prior to each injection. Directions for performing an airshot and setting the dose are provided in your insulin delivery device instruction manual.
5. Discard needle after each dose. The needle should not be recapped to avoid needlesticks. After each injection, patients must remove the needle without recapping and dispose of it in a puncture-resistant container. Used syringes, needles, or lancets should be placed in sharps containers (such as red biohazard containers), hard plastic containers (such as detergent bottles), or metal containers (such as an empty coffee can). Such containers should be sealed and disposed of properly.

After the first use of PenFill® cartridge:

1. Airshots should be done prior to each injection. Directions for performing an airshot and setting the dose are provided in your insulin delivery device instruction manual.
2. To avoid needle sticks, do not recap the needle. Throw away the needle safely after each injection

How should I inject LEVEMIR insulin with a syringe or 3 mL PenFill® cartridge compatible delivery device*?

1. Pinch your skin between two fingers, push the needle into the skinfold, and push the plunger to inject the insulin under your skin. The needle should be perpendicular to the skin. This means the needle will be straight in.
2. Keep the needle under your skin for at least 6 seconds to make sure you have injected all the insulin.
3. If blood appears after you pull the needle from your skin, press the injection site lightly with a finger. Do not rub the area.

* LEVEMIR PenFill® cartridges are for use with Novo Nordisk 3 mL PenFill® cartridge compatible insulin delivery devices and NovoFine® disposable needles.
INSTRUCTIONS FOR USE
Levemir® 3 mL InnoLet (100 units/mL, U-100)
LEVEMIR InnoLet (3 mL) directions for use
LEVEMIR InnoLet is a disposable dial-a-dose insulin delivery system able to deliver 1 to a maximum of 50 units. The dose can be adjusted in increments of 1 unit. LEVEMIR InnoLet is designed for use with NovoFine® single-use needles. LEVEMIR InnoLet is not recommended for the blind or severely visually impaired patients without the assistance of a sighted individual trained in the proper use of the product.
Please read and follow these instructions completely each time you use this device. If you do not follow these instructions completely, you may get too much or too little insulin.
Every time you give an injection using LEVEMIR InnoLet:

- Use a new needle
- Prime to make sure the InnoLet is ready to dose
- Make sure you got your full dose

Figure of Innolet and Needles
1. PREPARING THE LEVEMIR INNOLET
a. Pull off the cap.
b. Wipe the rubber membrane with an alcohol swab.
Figure 1A: Attaching needle to Innolet
c. Remove the protective tab from the disposable needle and screw the needle onto the InnoLet (see diagram 1A). Never place a disposable needle on your InnoLet until you are ready to give an injection. Remove the needle from InnoLet immediately after the use. If the needle is not removed, some liquid may leak from the LEVEMIR InnoLet.
d. Giving the air shot before each injection
Small amounts of air may collect in the needle and insulin reservoir during normal use. To avoid injecting air and to ensure proper dosing, dial 2 units by turning the dose selector clockwise. Hold the LEVEMIR InnoLet with the needle pointing up and tap the LEVEMIR InnoLet gently with your finger so any air bubbles collect in the top of the reservoir. Remove both the plastic outer and inner needle cap.
Figure 1B: Doing the air shot
e. With the needle pointing up, press the push button as far as it will go and the dose selector returns to zero. See if a drop of insulin appears at the needle tip (see Figure 1B). If not, repeat the procedure until insulin appears.
Before the first use of LEVEMIR InnoLet, you may need to perform up to 6 airshots to get a droplet of insulin at the needle tip. If you need to make more than 6 airshots, do not use the LEVEMIR InnoLet, and contact Novo Nordisk® at 1-800-727-6500. A small air bubble may remain but it will not be injected because the operating mechanism prevents the reservoir from being completely emptied.
2. SETTING THE DOSE
Figure 2: Setting the dose
Always check that the push button is fully depressed and the dose selector is set at 0. Hold the LEVEMIR InnoLet® in front of you and dial the dose selector clockwise to set the required dose. Do not put your hand over the push button when dialing the dose. If the button is not allowed to rise freely, insulin will be pushed out of the needle. You will hear a click for every single unit dialed. Do not rely on the clicking sound as a means for setting your dose. If you have set a wrong dose, simply dial the dose selector forward or backwards until the right number of dose has been set.
50 units is the maximum dose.
3. GIVING THE INJECTION
Use the injection technique recommended by your doctor or health care professionals.
a. Check that you have set the proper dose and depress the push button as far as it will go. Make sure not to block the dose selector while injecting, as the dose selector must be allowed to return to zero when you press the push button. When depressing the push button, you may hear a clicking sound. Do not rely on this clicking sound as a means of confirming delivery of your dose.
After making the injection, unscrew the needle and discard appropriately. After each injection, you must remove the needle before replacing the device cap and dispose of the needle in a puncture-resistant container. Used syringes, needles, or lancets should be placed in “sharps” containers (such as red biohazard containers), hard plastic containers (such as detergent bottles), or metal containers (such as an empty coffee can). Such containers should be sealed and disposed of properly.
It is important that you use a new needle for each injection. Health care professionals, relatives, and other caregivers, should follow general precautionary measures for removal and disposal of needles to eliminate the risk of unintended needlestick.
Figure 3: Giving the injection
4. LATER (SUBSEQUENT) INJECTIONS
Always check that the push button is fully depressed before using the LEVEMIR InnoLet® again. If not, turn the dose selector until the push button is completely down. Then proceed as stated in steps 1-3.
The numbers on the insulin reservoir can be used to estimate the amount of insulin left in the LEVEMIR InnoLet. Do not use these numbers to measure the insulin dose. You cannot set a dose greater than the number of units remaining in the reservoir.
5. FUNCTION CHECK
If you think that your LEVEMIR InnoLet is not working properly, follow this procedure:
a. Screw on a new NovoFine needle
b. Perform air shot as described in 1. PREPARING THE LEVEMIR INNOLET®, steps (d) through (e) and Figure 1B
c. Put the outer needle cap onto the needle
d. Dispense 20 units into the needle cap.
Figure of doing the function check
The insulin will fill the lower part of the cap (as shown in the figure above).
If the LEVEMIR InnoLet has released too much or too little insulin, repeat the test. If it happens again, do not use your LEVEMIR InnoLet and contact Novo Nordisk at 1-800-727-6500.
6. IMPORTANT NOTES

- If you need to perform more than 6 air shots before the first use of the disposable LEVEMIR InnoLet to get a droplet of insulin at the needle tip, do not use your LEVEMIR InnoLet and contact Novo Nordisk at 1-800-727-6500.
- Remember to perform an air shot before each injection. See figure 1B.
- Do not drop, damage, or crush the disposable LEVEMIR InnoLet.
- Remember to keep the disposable LEVEMIR InnoLet with you. Don’t leave it in a car or other location where it can get too hot or too cold.
- LEVEMIR InnoLet is not supplied with needles. NovoFine® disposable needles are designed and recommended for use with Novo Nordisk® insulin delivery devices, including LEVEMIR InnoLet.
- Never place a disposable needle on the LEVEMIR InnoLet until you are ready to use it. Remove the needle right after the use without recapping.
- Discard the needle after each injection. After each injection, remove the needle before replacing the device cap and dispose the needle in a puncture-resistant container. Used syringes, needles, or lancets should be placed in “sharps” containers (such as red biohazard containers), hard plastic containers (such as detergent bottles), or metal containers (such as an empty coffee can). Such containers should be sealed and disposed of properly.
- Throw away the empty LEVEMIR InnoLet without the needle attached.
- Always carry an extra LEVEMIR InnoLet with you in case your LEVEMIR InnoLet you are using is damaged or lost.
- To avoid possible transmission of disease, do not share your LEVEMIR InnoLet with anyone, even if you attach a new needle.
- Novo Nordisk is not responsible for harm due to using this insulin delivery system with products not recommended by Novo Nordisk.
- Keep this disposable LEVEMIR InnoLet out of the reach of children.

INSTRUCTIONS FOR USE
LEVEMIR® FlexPen®
Introduction
Please read the following instructions carefully before using your Levemir® FlexPen®.
Levemir FlexPen is a disposable dial-a-dose insulin pen. You can select doses from 1 to 60 units in increments of 1 unit. Levemir FlexPen is designed to be used with NovoFine® needles.
Δ Levemir FlexPen should not be used by people who are blind or have severe visual problems without the help of a person who has good eyesight and who is trained to use the Levemir FlexPen the right way.
Getting ready
Make sure you have the following items:

- Levemir FlexPen
- New NovoFine needle
- Alcohol swab

Figure of Levemir FlexPen and Needle
Preparing your Levemir FlexPen
Wash your hands with soap and water. Before you start to prepare your injection, check the label to make sure that you are taking the right type of insulin. This is especially important if you take more than 1 type of insulin. Levemir should look clear.
A. Pull off the pen cap (see diagram A).
Diagram A: Pull the cap off the FlexPen
Wipe the rubber stopper with an alcohol swab.
B. Attaching the needle
Remove the protective tab from a disposable needle.
Screw the needle tightly onto your FlexPen. It is important that the needle is put on straight (see diagram B).
Diagram B: Attaching the needle to FlexPen
Never place a disposable needle on your Levemir FlexPen until you are ready to take your injection.
C. Pull off the big outer needle cap (see diagram C).
Diagram C: Removing the big outer needle cap
D. Pull off the inner needle cap and dispose of it (see diagram D).
Diagram D: Removing the inner needle cap
Δ Always use a new needle for each injection to help ensure sterility and prevent blocked needles.
Δ Be careful not to bend or damage the needle before use.
Δ To reduce the risk of unexpected needle sticks, never put the inner needle cap back on the needle.
Giving the airshot before each injection:
Before each injection small amounts of air may collect in the cartridge during normal use. To avoid injecting air and to ensure proper dosing:
E. Turn the dose selector to select 2 units (see diagram E).
Diagram E: Selecting the dose for the air shot
F. Hold your Levemir FlexPen with the needle pointing up. Tap the cartridge gently with your finger a few times to make any air bubbles collect at the top of the cartridge (see diagram F).
Diagram F: Tap the cartridge to move air to top
G. Keep the needle pointing upwards, press the push-button all the way in (see diagram G). The dose selector returns to 0.
Diagram G: Point needle upwards and press the push-button
A drop of insulin should appear at the needle tip. If not, change the needle and repeat the procedure no more than 6 times.
If you do not see a drop of insulin after 6 times, do not use the Levemir FlexPen and contact Novo Nordisk at 1-800-727-6500.
A small air bubble may remain at the needle tip, but it will not be injected.
Selecting your dose
Check and make sure that the dose selector is set at 0.
H. Turn the dose selector to the number of units you need to inject. The pointer should line up with your dose.
The dose can be corrected either up or down by turning the dose selector in either direction until the correct dose lines up with the pointer (see diagram H). When turning the dose selector, be careful not to press the push-button as insulin will come out.
Diagram H: Selecting your dose
I. Insert the needle into your skin.
Inject the dose by pressing the push-button all the way in until the 0 lines up with the pointer (see diagram I). Be careful only to push the button when injecting.
Diagram I: Giving the injection
J. Keep the needle in the skin for at least 6 seconds, and keep the push-button pressed all the way in until the needle has been pulled out from the skin (see diagram J).
Diagram J: Keep needle in skin for 6 seconds
This will make sure that the full dose has been given. You may see a drop of Levemir at the needle tip. This is normal and has no effect on the dose you just received. If blood appears after you take the needle out of your skin, press the injection site lightly with a finger. Do not rub the area.
After the injection
Do not recap the needle. Recapping can lead to a needle stick injury. Remove the needle from the Levemir FlexPen after each injection. This helps to prevent infection, leakage of insulin, and will help to make sure you inject the right dose of insulin.
The Levemir FlexPen prevents the cartridge from being completely emptied. It is designed to deliver 300 units.
Δ Put the needle and any empty Levemir FlexPen or any used Levemir FlexPen still containing insulin in a sharps container or some type of hard plastic or metal container with a screw top such as a detergent bottle or empty coffee can. These containers should be sealed and thrown away the right way. Check with your healthcare provider about the right way to throw away used syringes and needles. There may be local or state laws about how to throw away used needles and syringes. Do not throw away used needles and syringes in household trash or recycling bins.
K. Put the pen cap on the Levemir FlexPen and store the Levemir FlexPen without the needle attached (see diagram K).
Diagram K: Replacing the pen cap
Function Check
If your Levemir FlexPen is not working the right way, follow the steps below:
L.

- Screw on a new NovoFine needle.
- Remove the big outer needle cap and the inner needle cap.
- Do an airshot as described in “Giving the airshot before each injection”.
- Put the big outer needle cap onto the needle. Do not put on the inner needle cap.
- Turn the dose selector so the dose indicator window shows 20 units.
- Hold the Levemir FlexPen so the needle is pointing down.
- Press the push-button all the way in.

The insulin should fill the lower part of the big outer needle cap (see diagram L). If Levemir FlexPen has released too much or too little insulin, do the function check again. If the same problem happens again, do not use your Levemir FlexPen and contact Novo Nordisk at 1-800-727-6500.
Diagram L: Figure of function check
Maintenance
Your FlexPen is designed to work accurately and safely. It must be handled with care. Avoid dropping your FlexPen as it may damage it. If you are concerned that your FlexPen is damaged, use a new one. You can clean the outside of your FlexPen by wiping it with a damp cloth. Do not soak or wash your FlexPen as it may damage it. Do not refill your FlexPen.
Δ Remove the needle from the Levemir FlexPen after each injection. This helps to ensure sterility, prevent leakage of insulin, and will help to make sure you inject the right dose of insulin for future injections.
Δ Be careful when handling used needles to avoid needle sticks and transfer of infectious diseases.
Δ Keep your Levemir FlexPen and needles out of the reach of children.
Δ Use Levemir FlexPen as directed to treat your diabetes. Needles and Levemir FlexPen must not be shared.
Δ Always use a new needle for each injection.
Δ Novo Nordisk is not responsible for harm due to using this insulin pen with products not recommended by Novo Nordisk.
Δ As a precautionary measure, always carry a spare insulin delivery device in case your Levemir FlexPen is lost or damaged.
Δ Remember to keep the disposable Levemir FlexPen with you. Do not leave it in a car or other location where it can get too hot or too cold.

PRINCIPAL DISPLAY PANEL

Levemir®
Insulin detemir (rDNA origin) injection
NDC 68258-8977-01
List 368712
100 units/mL (U-100)
10 mL
For subcutaneous use only
Rx Only